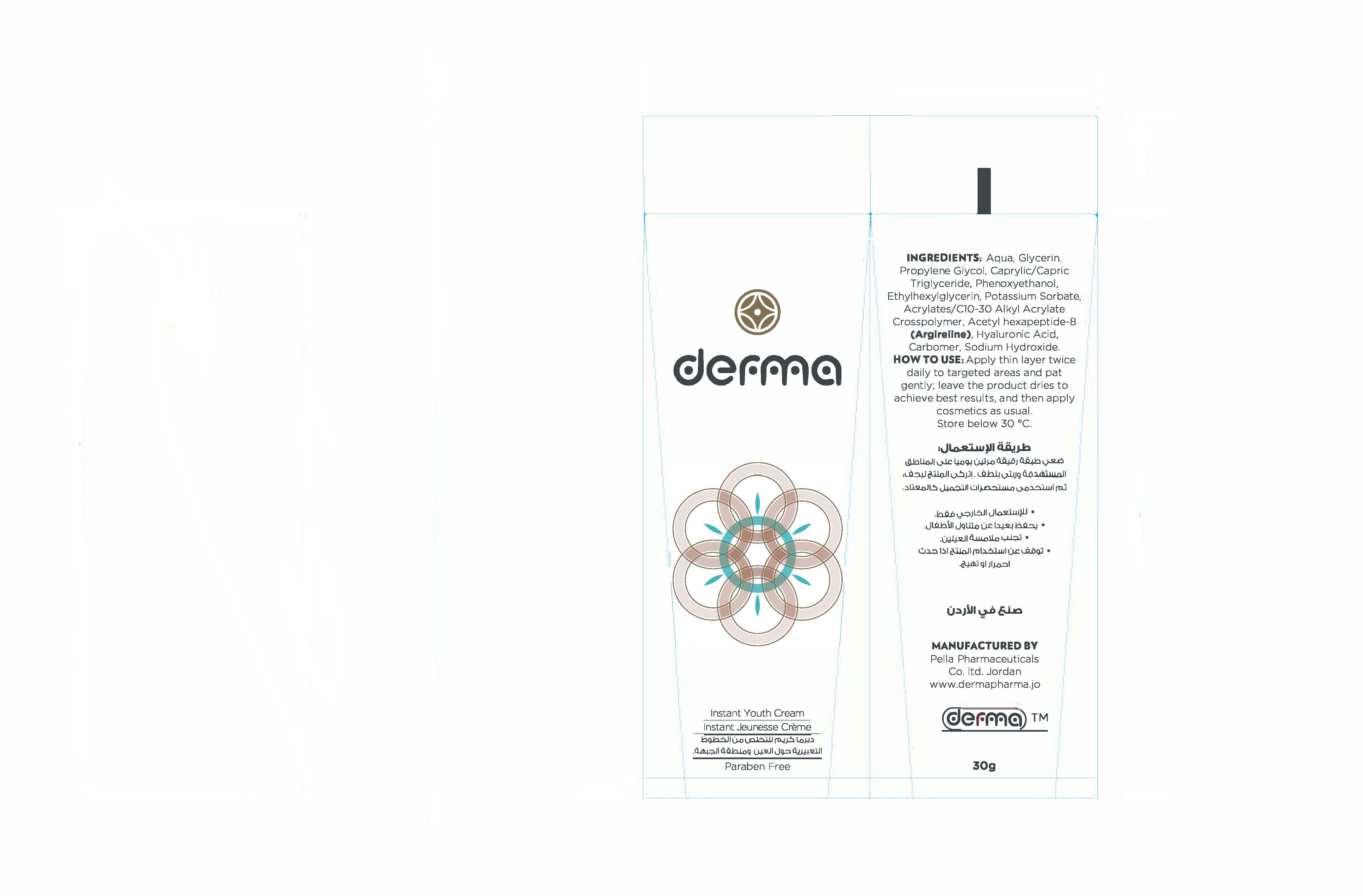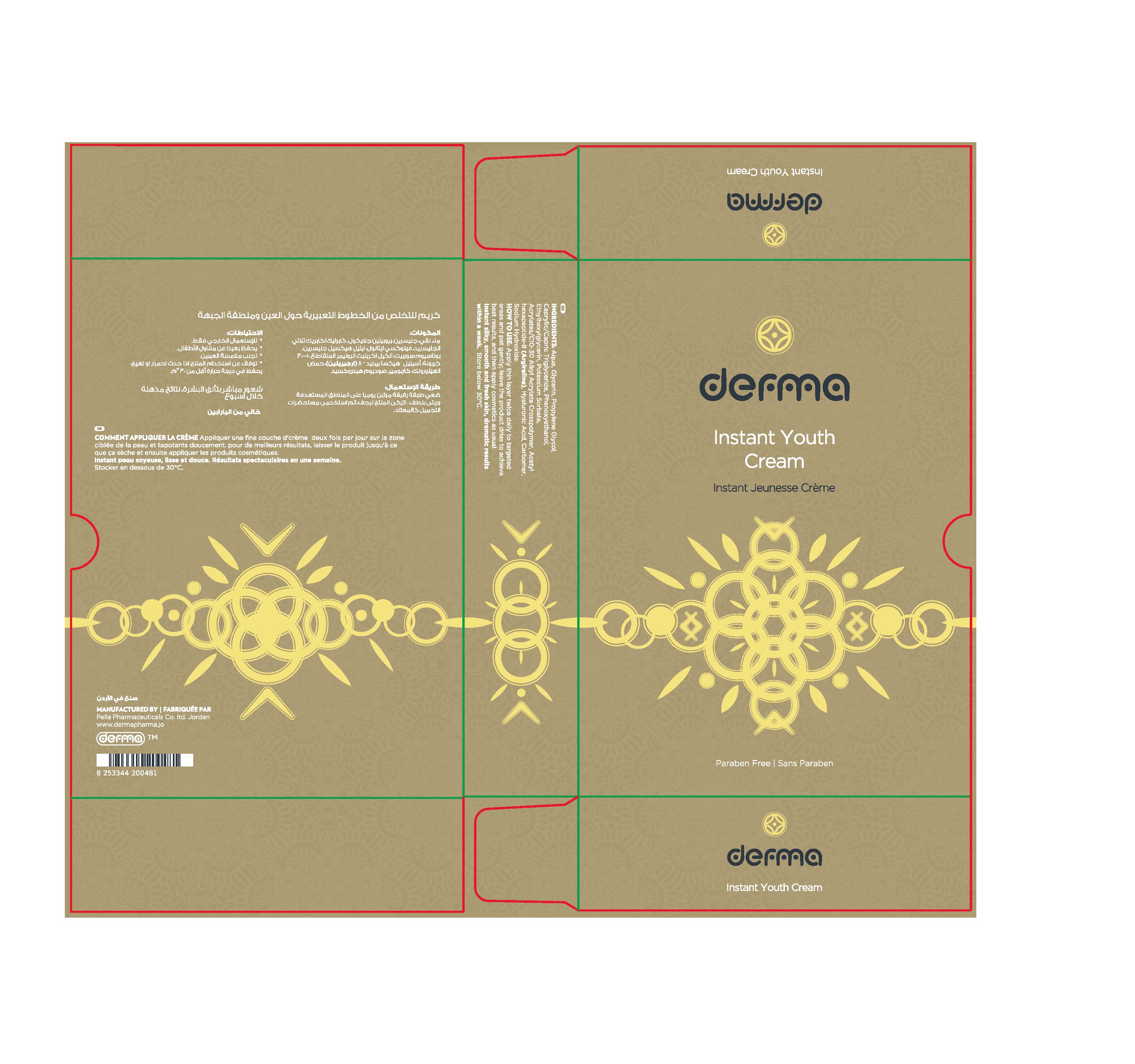 DRUG LABEL: Derma Instant Youth
NDC: 82160-481 | Form: CREAM
Manufacturer: Pella Pharmaceuticals Co. Ltd
Category: otc | Type: HUMAN OTC DRUG LABEL
Date: 20211202

ACTIVE INGREDIENTS: HYALURONIC ACID 0.3 mg/30 g; ACETYL HEXAPEPTIDE-8 0.015 mg/30 g
INACTIVE INGREDIENTS: PHENOXYETHANOL; MEDIUM-CHAIN TRIGLYCERIDES; PROPYLENE GLYCOL; CARBOMER 940; CARBOMER INTERPOLYMER TYPE A (ALLYL SUCROSE CROSSLINKED); POTASSIUM SORBATE; GLYCERIN; SODIUM HYDROXIDE; ETHYLHEXYLGLYCERIN; WATER

Instant Youth

Forms and presentation

Cream: Tube of 30 g.

Active ingredients

Hyaluronic Acid

Acetyl hexapeptide-8

Inactive ingredients

Aqua, Glycerin, Propylene Glycol, Caprylic/Capric Triglyceride, Phenoxyethanol, Ethylhexylglycerin, Potassium Sorbate, Acrylates/Cl0- 30 Alkyl Acrylate Crosspolymer, Carbomer, Sodium Hydroxide.

Purpose

Anti-wrinkles

Properties

It is a cream with an Instant silky, smooth and fresh skin. Dramatic results within a week.
Paraben free.

Indications

It is a cream diminishes the appearance of fine lines and wrinkles around eyes and forehead.

Precautions

Keep out of reach of children

Warnings

- For external use only
- Avoid contact with eyes

Contraindications

Hypersensitivity to any of the components.

Side effects

There are no known side effects.

Dosage and administration

Apply thin layer twice daily to targeted areas and pat gently; leave the product dries to achieve best results, and then apply cosmetics as usual.

Storage conditions

Store at a temperature below 30 °C.